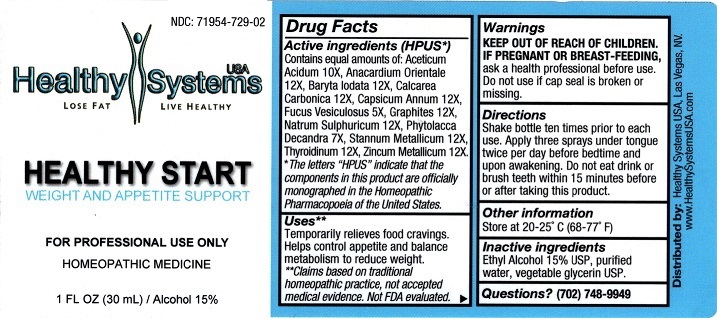 DRUG LABEL: Healthy Start Weight and Appetite Support
NDC: 71954-729 | Form: LIQUID
Manufacturer: WELL BODY CONCEPTS LLC
Category: homeopathic | Type: HUMAN PRESCRIPTION DRUG LABEL
Date: 20211229

ACTIVE INGREDIENTS: ACETIC ACID 10 [hp_X]/30 mL; SEMECARPUS ANACARDIUM JUICE 12 [hp_X]/30 mL; BARIUM IODIDE 12 [hp_X]/30 mL; OYSTER SHELL CALCIUM CARBONATE, CRUDE 12 [hp_X]/30 mL; CAPSICUM 12 [hp_X]/30 mL; FUCUS VESICULOSUS 5 [hp_X]/30 mL; GRAPHITE 12 [hp_X]/30 mL; SODIUM SULFATE 12 [hp_X]/30 mL; PHYTOLACCA AMERICANA ROOT 7 [hp_X]/30 mL; TIN 12 [hp_X]/30 mL; THYROID, UNSPECIFIED 12 [hp_X]/30 mL; ZINC 12 [hp_X]/30 mL
INACTIVE INGREDIENTS: ALCOHOL; WATER; GLYCERIN

Healthy Start Weight and Appetite Support

Active ingredients (HPUS*)

Contains equal amounts of: Aceticum Acidum 10X, Anacardium Orientale 12X, Baryta Iodata 12X, Calcarea Carbonica 12X, Capsicum Annum 12X,

Fucus Vesiculosus 5X Graphites 12X, Natrum Sulphuricum 12X Phytolacca Decandra 7X, Stannum Metallicum 12X, Thyroidinum 12X, Zincum Metallicum 12X.

* The letters "HPUS" indicate that the components in this product are officially monographed in the Homeopathic Pharmacopoeia of the United States.

INDICATIONS AND USAGE

Uses** Temporarily relieves food cravings. Helps control appetite and balance metabolism to reduce weight.

** Claims based on traditional homeopathic practice, not accepted medical evidence. Not FDA evaluated.

KEEP OUT OF REACH OF CHILDREN.

IF PREGNANT OR BREAST-FEEDING.

ask a health professional before use.

Do not use if cap seal is broken or missing.

KEEP OUT OF REACH OF CHILDREN.

DOSAGE AND ADMINISTRATION

DirectionsShake bottle ten times prior to each use. Apply three sprays under tongue twice per day before bedtime and upon awakening. Do not eat drink or brush teeth within 15 minutes before or after taking this product.

Other information

Store at 20-25ºC (68-77ºF)

INACTIVE INGREDIENT

Inactive ingredients Ethyl Alcohol 15% USP, purified water, vegetable glycerin USP.

Questions? (702) 748-9949

PACKAGE LABEL

NDC: 71954-729-02

USA

Healthy Systems

LOSE FAT LIVE HEALTHY

HEALTHY START

WEIGHT AND APPETITE SUPPORT

FOR PROFESSIONAL USE ONLY

HOMEOPATHIC MEDICINE

1 FL OZ (30mL) / Alcohol 15%